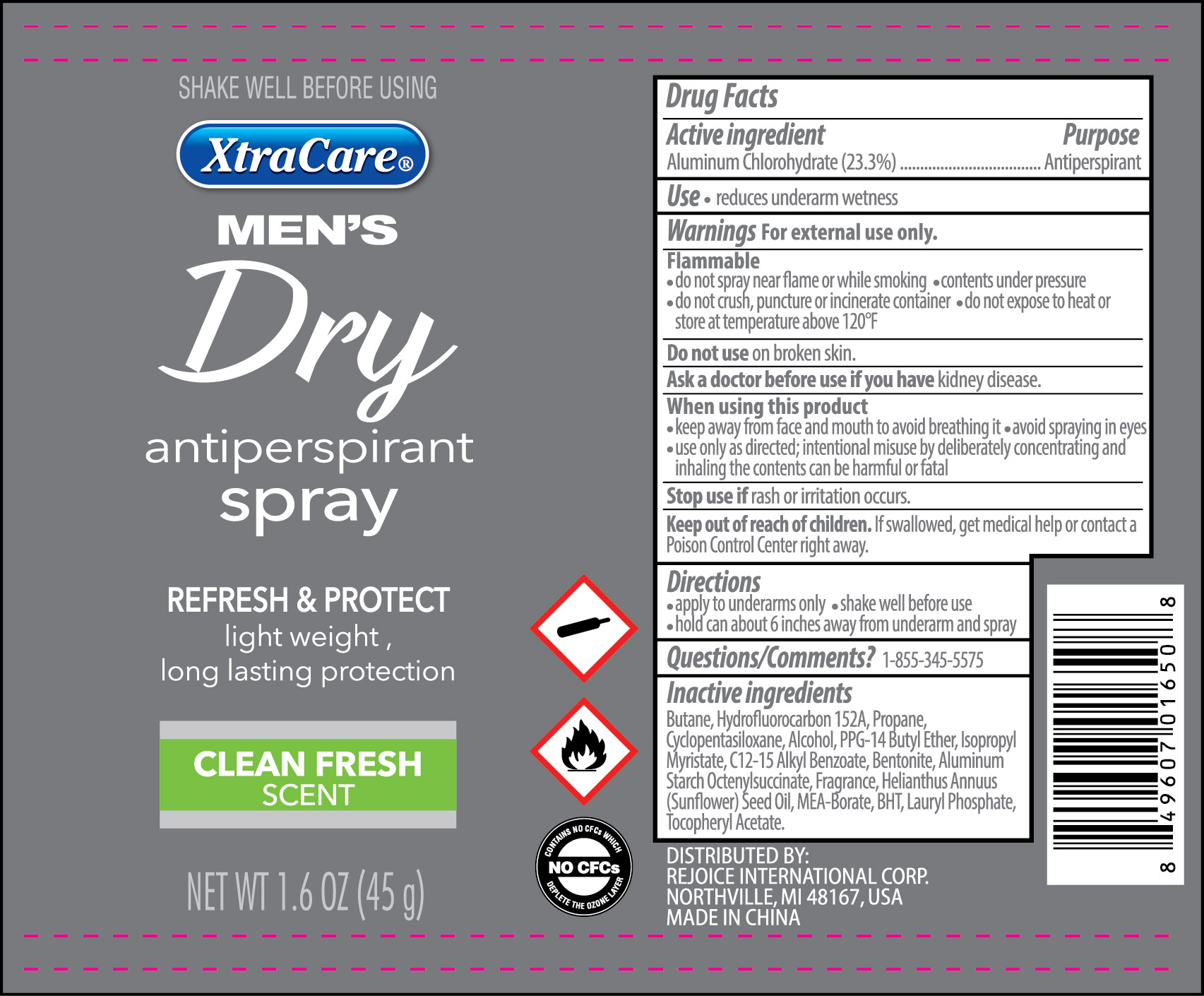 DRUG LABEL: Antiperspirant Dry 1.6 oz Men
NDC: 57337-109 | Form: AEROSOL, SPRAY
Manufacturer: Rejoice International Inc
Category: otc | Type: HUMAN OTC DRUG LABEL
Date: 20250213

ACTIVE INGREDIENTS: ALUMINUM CHLOROHYDRATE 23.3 g/100 g
INACTIVE INGREDIENTS: PPG-14 BUTYL ETHER; ALKYL (C12-15) BENZOATE; PROPANE; BENTONITE; 1,1-DIFLUOROETHANE; CYCLOMETHICONE 5; ALCOHOL; BUTYLATED HYDROXYTOLUENE; DISTEARDIMONIUM HECTORITE; .ALPHA.-TOCOPHEROL ACETATE; SUNFLOWER OIL; BUTANE; ISOPROPYL MYRISTATE; ALUMINUM STARCH OCTENYLSUCCINATE; DIMETHICONE

Antiperspirant Dry Spray 1.6 oz Men

Active Ingredient ........................................................................... Purpose

Aluminum Chlorohydrate 23.3% .................................................. Antiperspirant

PURPOSE

Antiperspirant

Keep out of reach of children. If swallowed, get medical help or contact a Poison Control Center right away.

INDICATIONS AND USAGE

Reduces underarm wetness

Warnings

For external use only.

Flammable. Do not use while smoking or near heat or flame or while smoking. Can cause serious injury or death.

- Keep away from face and mouth to avoid breathing in.
- Avoid spraying in eyes. CONTENTS UNDER PRESSURE. Do not puncture or incinerate. Do not expose to heat or store at temperatures above 120oF/50oC or in enclosed places that could overheat.
- Do not use on broken skin.
- Ask a doctor before using, if you have kidney disease
- When using this product.
- Keep away from face and mouth to avoid breathing it
- avoid spraying in eyes
- USE ONLY AS DIRECTED. INTENTIONAL MISSUSE BY DELIBERATELY CONCENTRATING AND INHAILING THE CONTENTS CAN BE HARMFUL OR FATAL.
- Stop use if rash or irritation occurs

Directions

- For underarm use only. Shake can well before each use. Hold can 6 inches away from skin. Spray underarm and spray

Inactive Ingredients

Isobutane, Butane, Hydrofluorocarbon 152a, Cyclopentasiloxane, Alcohol, PPG-14 Butyl Ether, Helianthus Annuus Seed Oil, Isopropryl Myristate, C12-15 Alkyl Benzoate, Frangrance, Propane, Aluminum Starch Ocetenylsuccinate, Disteardimonium Hectorite, Dimethicone, Tocopheryl Acetate, BHT, Bentonite, Lauryl Phosphate